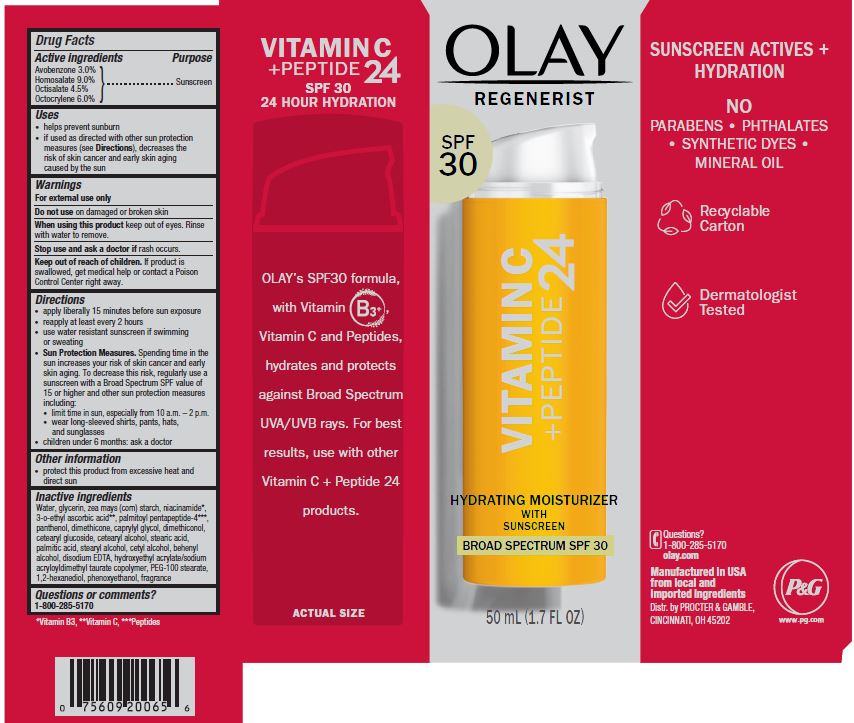 DRUG LABEL: Olay Regenerist Vitamin C plus Peptide 24 Hydrating  Moisturizer
NDC: 69423-606 | Form: CREAM
Manufacturer: The Procter & Gamble Manufacturing Company
Category: otc | Type: HUMAN OTC DRUG LABEL
Date: 20251231

ACTIVE INGREDIENTS: OCTISALATE 4.5 g/100 mL; OCTOCRYLENE 6 g/100 mL; AVOBENZONE 3 g/100 mL; HOMOSALATE 9 g/100 mL
INACTIVE INGREDIENTS: 3-O-ETHYL ASCORBIC ACID; HYDROXYETHYL ACRYLATE/SODIUM ACRYLOYLDIMETHYL TAURATE COPOLYMER (100000 MPA.S AT 1.5%); PALMITIC ACID; WATER; GLYCERIN; NIACINAMIDE; DIMETHICONE; PANTHENOL; STARCH, CORN; PALMITOYL PENTAPEPTIDE-4; PEG-100 STEARATE; CETEARYL GLUCOSIDE; CETOSTEARYL ALCOHOL; STEARYL ALCOHOL; DOCOSANOL; CETYL ALCOHOL; CAPRYLYL GLYCOL; 1,2-HEXANEDIOL; PHENOXYETHANOL; STEARIC ACID; EDETATE DISODIUM; DIMETHICONOL GUM

Olay® Regenerist® Vitamin C + Peptide 24 Hydrating Moisturizer
Broad Spectrum SPF 30

Drug Facts

ACTIVE INGREDIENT

AVOBENZONE 3.0%

HOMOSALATE 9.0%

OCTISALATE 4.5%

OCTOCRYLENE 6.0%

PURPOSE

Sunscreen

Sunscreen

Sunscreen

Sunscreen

Uses

- helps prevent sunburn
- if used as directed with other sun protection measures (see Directions), decreases the risk of skin cancer and early skin aging caused by the sun

Warnings

For external use only

Do not use

- on damaged or broken skin

When using this product

- keep out of eyes. Rinse with water to remove.

Stop use and ask a doctor if

- rash occurs

Keep out of reach of children. If product is swallowed, get medical help or contact a Poison Control Center right away.

Directions

- apply liberally 15 minutes before sun exposure
- reapply at least every 2 hours
- use water resistant sunscreen if swimming or sweating
- Sun Protection Measures. Spending time in the sun increases your risk of skin cancer and early skin aging. To decrease this risk, regularly use a sunscreen with a Broad Spectrum SPF value of 15 or higher and other sun protection measures including:
  - limit time in sun, especially from 10 a.m. - 2 p.m.
  - wear long-sleeved shirts, pants, hats, and sunglasses
- children under 6 months: ask a doctor

Other information

- protect this product from excessive heat and direct sun

Inactive ingredients

Water, glycerin, zea mays (corn) starch, niacinamide*, 3-o-ethyl ascorbic acid**, palmitoyl pentapeptide-4***, panthenol, dimethicone, caprylyl glycol, dimethiconol, cetearyl glucoside, cetearyl alcohol, stearic acid, palmitic acid, stearyl alcohol, cetyl alcohol, behenyl alcohol, disodium EDTA, hydroxyethyl acrylate/sodium acryloyldimethyl taurate copolymer, PEG-100 stearate, 1,2-hexanediol, phenoxyethanol, fragrance

Questions or comments?

Call 1-800-285-5170

Distr. by PROCTER & GAMBLE,
CINCINNATI, OH 45202

PRINCIPAL DISPLAY PANEL - 50 mL CARTON

Olay ®

REGENERIST ®

VITAMIN C + PEPTIDE24

HYDRATING MOISTURIZER

WITH SUNSCREEN

BROAD SPECTRUM SPF 30

50 mL (1.7 FL OZ)